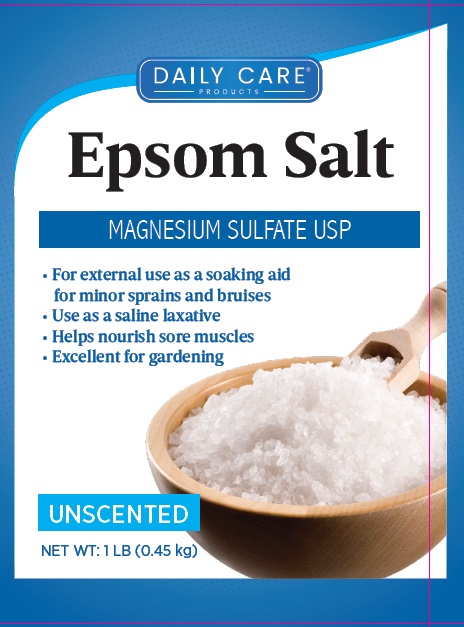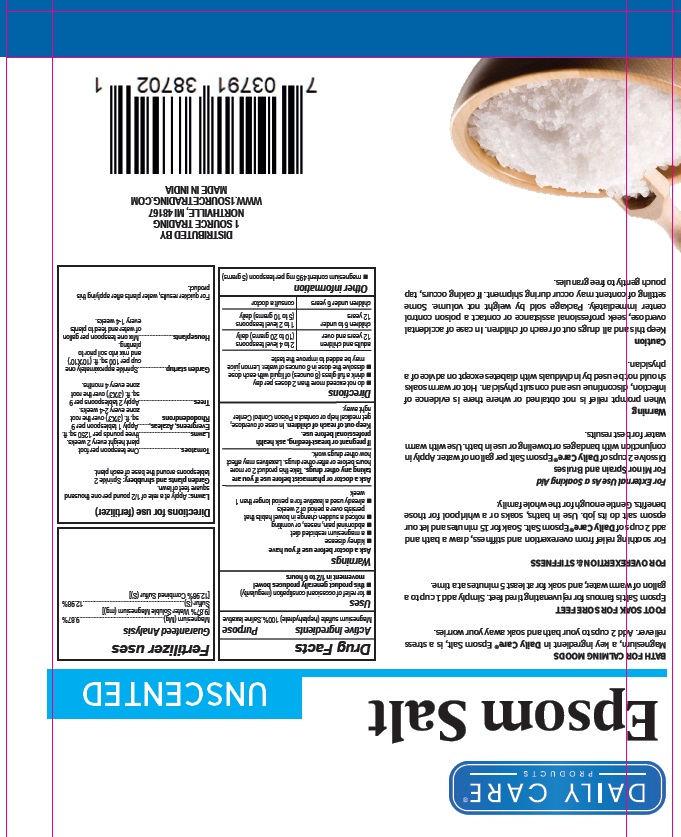 DRUG LABEL: Daily Care Epsom Salt
NDC: 78107-001 | Form: GRANULE
Manufacturer: 1 SOURCE TRADING LLC
Category: otc | Type: HUMAN OTC DRUG LABEL
Date: 20210603

ACTIVE INGREDIENTS: MAGNESIUM SULFATE HEPTAHYDRATE 100 g/100 g
INACTIVE INGREDIENTS: WATER

Daily Care Epsom Salt

Active Ingredients Purpose
Magnesium Sulfate (heptahydrate) 100% Saline laxative

Uses

- For relief of occasional constipation (irregularity)
- this product generally produces bowel movement in 1/2 to 6 hours

KEEP OUT OF REACH OF CHILDREN

If pregnant or bread feeding, aska a health professional before use. Keep out of reach of children. In Case of overdose, get medical help or contact a Poison Control Center right away.

Ask a doctor or pharmacist before use if your are taking any other drug. Take this product 2 or more hours before or after other drugs. Laxatives may affect how other drugs work.

Warnings

Ask a doctor before use if you have

- kidney disease
- a magnesium restricted diet
- abdominal pain, nausea, or vomiting
- noticed a sudden change in bowel habits that persists over a period of 2 weeks
- already used a laxative for a period longer than 1 week

Directions

- do not exceed more than 2 doses per day
- drink a full glass (8 ounces) of liquid with each dose
- dissolve the dose in 8 ounces of water. Lemon juice may be added to improve the taste.

adults and children 12 years and over - 2 to 4 level teaspoons (10 to 20 grams) daily

children 6 to under 12 year - 1 to 2 level teaspoons (5 to 10 grams) daily

children under 6 year - consult a doctor

INACTIVE INGREDIENT

None Available